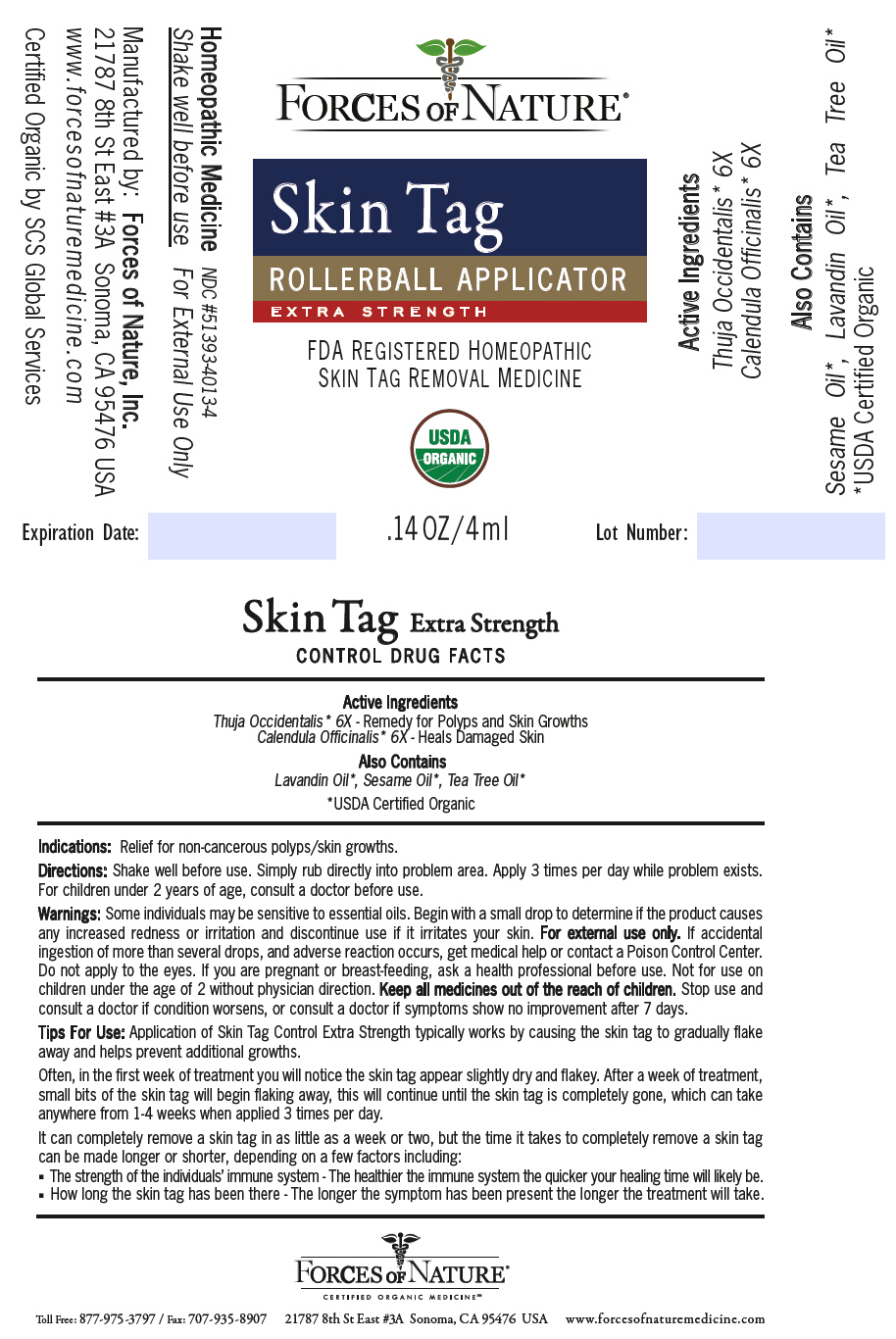 DRUG LABEL: Skin Tags
NDC: 51393-4013 | Form: SOLUTION/ DROPS
Manufacturer: Forces of Nature
Category: homeopathic | Type: HUMAN OTC DRUG LABEL
Date: 20200429

ACTIVE INGREDIENTS: Thuja Occidentalis Leafy Twig 6 [hp_X]/100 mL; Calendula Officinalis Whole 6 [hp_X]/100 mL
INACTIVE INGREDIENTS: Sesame Oil; Lavender Oil; Tea Tree Oil

Skin Tags

DRUG FACTS

Active Ingredients

Thuja Occidentalis [USDA Certified Organic] 6X - Remedy for Polyps and Skin Growths

Calendula Officinalis 6X - Heals Damaged Skin

Also Contains

Lavandin Oil, Sesame Oil, Tea Tree Oil

Indications

PURPOSE

Relief for non-cancerous polyps/skin growths.

Directions

Shake well before use. Simply rub directly into problem area. Apply 3 times per day while problem exists. For children under 2 years of age, consult a doctor before use.

Warnings

Some individuals may be sensitive to essential oils. Begin with a small drop to determine if the product causes any increased redness or irritation and discontinue use if it irritates your skin. For external use only. If accidental ingestion of more than several drops, and adverse reaction occurs, get medical help or contact a Poison Control Center. Do not apply to the eyes. If you are pregnant or breast-feeding, ask a health professional before use. Not for use on children under the age of 2 without physician direction.

KEEP OUT OF REACH OF CHILDREN

Keep all medicines out of the reach of children.

Stop use and consult a doctor if condition worsens, or consult a doctor if symptoms show no improvement after 7 days.

Tips For Use

Application of Skin Tag Control Extra Strength typically works by causing the skin tag to gradually flake away and helps prevent additional growths.

Often, in the first week of treatment you will notice the skin tag appear slightly dry and flakey. After a week of treatment, small bits of the skin tag will begin flaking away, this will continue until the skin tag is completely gone, which can take anywhere from 1-4 weeks when applied 3 times per day.

It can completely remove a skin tag in as little as a week or two, but the time it takes to completely remove a skin tag can be made longer or shorter, depending on a few factors including:

- The strength of the individuals' immune system - The healthier the immune system the quicker your healing time will likely be.
- How long the skin tag has been there - The longer the symptom has been present the longer the treatment will take.

Manufactured by: Forces of Nature, Inc.
21787 8th St East #3A Sonoma, CA 95476 USA

PRINCIPAL DISPLAY PANEL - 4 ml Bottle Label

FORCES OF NATURE ®

Skin Tag
ROLLERBALL APPLICATOR
EXTRA STRENGTH

FDA REGISTERED HOMEOPATHIC
SKIN TAG REMOVAL MEDICINE

USDA
ORGANIC

.14 OZ/4ml